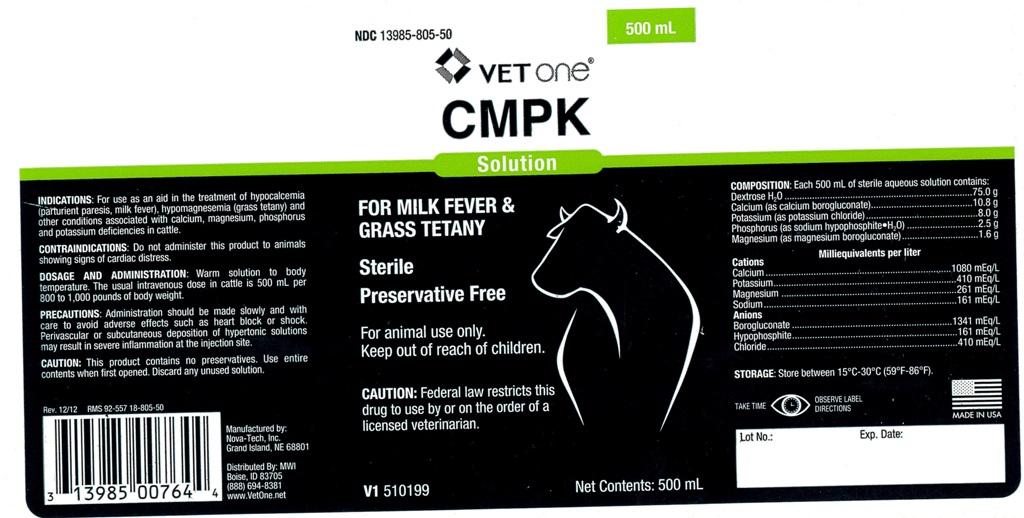 DRUG LABEL: CMPK
NDC: 13985-805 | Form: INJECTION, SOLUTION
Manufacturer: MWI (VetOne)
Category: animal | Type: PRESCRIPTION ANIMAL DRUG LABEL
Date: 20150901

ACTIVE INGREDIENTS: Calcium Gluconate Monohydrate 10.8 g/500 mL; Potassium Chloride 8.0 g/500 mL; Magnesium Gluconate 1.6 g/500 mL; SODIUM HYPOPHOSPHITE MONOHYDRATE 2.5 g/500 mL; DEXTROSE MONOHYDRATE 75.0 g/500 mL

CMPK Solution

COMPOSITION:

Each 500 mL of sterile aqueous solution contains:
Dextrose H2O.............................................................75.0 g
Calcium (as calcium borogluconate)..............................10.8 g
Potassium (as potassium chloride).................................8.0 g
Phosphorus (as sodium hypophosphite H2O)....................2.5 g
Magnesium (as magnesium borogluconate).....................1.6 g

Milliequivalents per liter
Cations
Calcium....................1080 mEq/L
Potassium..................410 mEq/L
Magnesium................261 mEq/L
Sodium.....................161 mEq/L
Anions
Borogluconate...........1341 mEq/L
Hypophosphite............161 mEq/L
Chloride.....................410 mEq/L

STORAGE:

Store between 15 degree C - 30 degree C (59 degree F - 86 degree F).

SAFE HANDLING WARNING

TAKE TIME OBSERVE LABEL DIRECTIONS

VETERINARY INDICATIONS

FOR MILK FEVER & GRASS TETANY

STERILE

Preservative Free

For animal use only.

Keep out of reach of children.

CAUTION:

Federal law restricts this drug to use by or on the order of a licensed veterinarian.

INDICATIONS:

For use as an aid in the treatment of hypocalcemia (parturient paresis, milk fever), hypomagnesemia (grass tetany) and other conditions associated with calcium, magnesium, phosphorus and potassium deficiencies in cattle.

CONTRAINDICATIONS:

Do not administer this product to animals showing signs of cardiac distress.

DOSAGE AND ADMINISTRATION:

Warm solution to body temperature. The usual intravenous dose in cattle is 500 mL per 800 to 1,000 pounds of body weight.

PRECAUTIONS:

Administration should be made slowly and with care to avoid adverse effects such as heart block or shock. Perivascular or subcutaneous deposition of hypertonic solutions may result in severe inflammation at the injection site.

CAUTION:

This product contains no preservatives. Use entire contents when first opened. Discard any unused solution.

INFORMATION FOR OWNERS/CAREGIVERS

Rev. 12/12 RMS 92-557 18-805-50

Manufactured by:
Nova-Tech, Inc.
Grand Island, NE 68801

Distributed By: MWI
Boise, ID 83705
(888)694-8381
www.VetOne.net

V1 510199 Net Contents: 500 mL

Lot No.: Exp. Date: